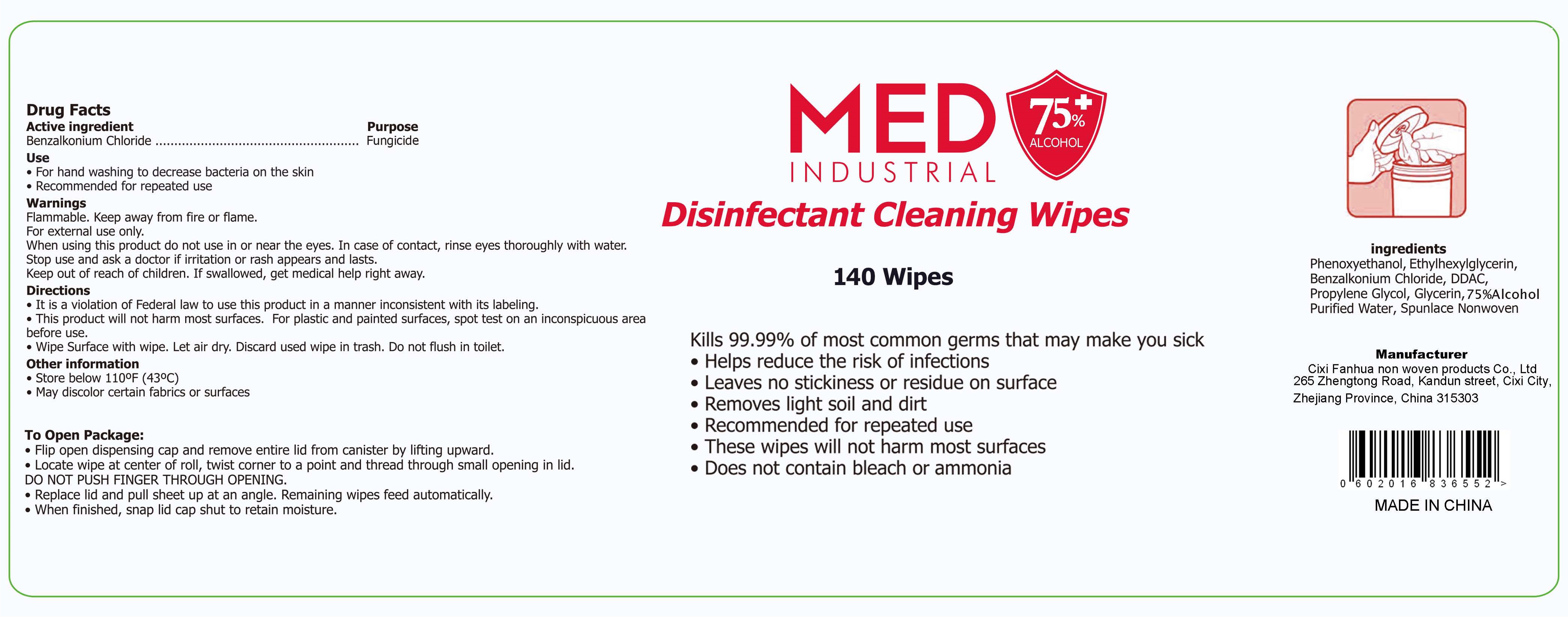 DRUG LABEL: Disinfectant Cleaning Wipes
NDC: 54826-002 | Form: CLOTH
Manufacturer: Cixi Fanhua Non Woven Products Co., Ltd
Category: otc | Type: HUMAN OTC DRUG LABEL
Date: 20200615

ACTIVE INGREDIENTS: ALCOHOL 588 mL/140 1
INACTIVE INGREDIENTS: WATER

DOSAGE AND ADMINISTRATION

●Store below 110°F (43°C)
●May discolor certain fabrics or surfaces

INACTIVE INGREDIENT

Non-woven fabric,

pure water

Quaternary Ammonium Salt

INDICATIONS AND USAGE

●Flip open dispensing cap and remove entire lid from canister by lifting upward.
●Locate wipe at center of roll, twist corner to a point and thread through small opening in lid.
DO NOT PUSH FINGER THROUGH OPENING.
●Replace lid and pull sheet up at an angle. Remaining wipes feed automatically.
●When finished, snap lid cap shut to retain moisture.

ACTIVE INGREDIENT

alcohol

keep out of reach of children

PURPOSE

Disinfection
Sterilization
No Rinseing

WARNINGS

Flammable. Keep away from fire or flame.For external use only.When using this product do not use in or near the eyes. In case of contact, rinse eyes thoroughly with water.Stop use and ask a doctor if iritation or rash appears and lasts.Keep out of reach of children. If swallowed, get medical help right away.